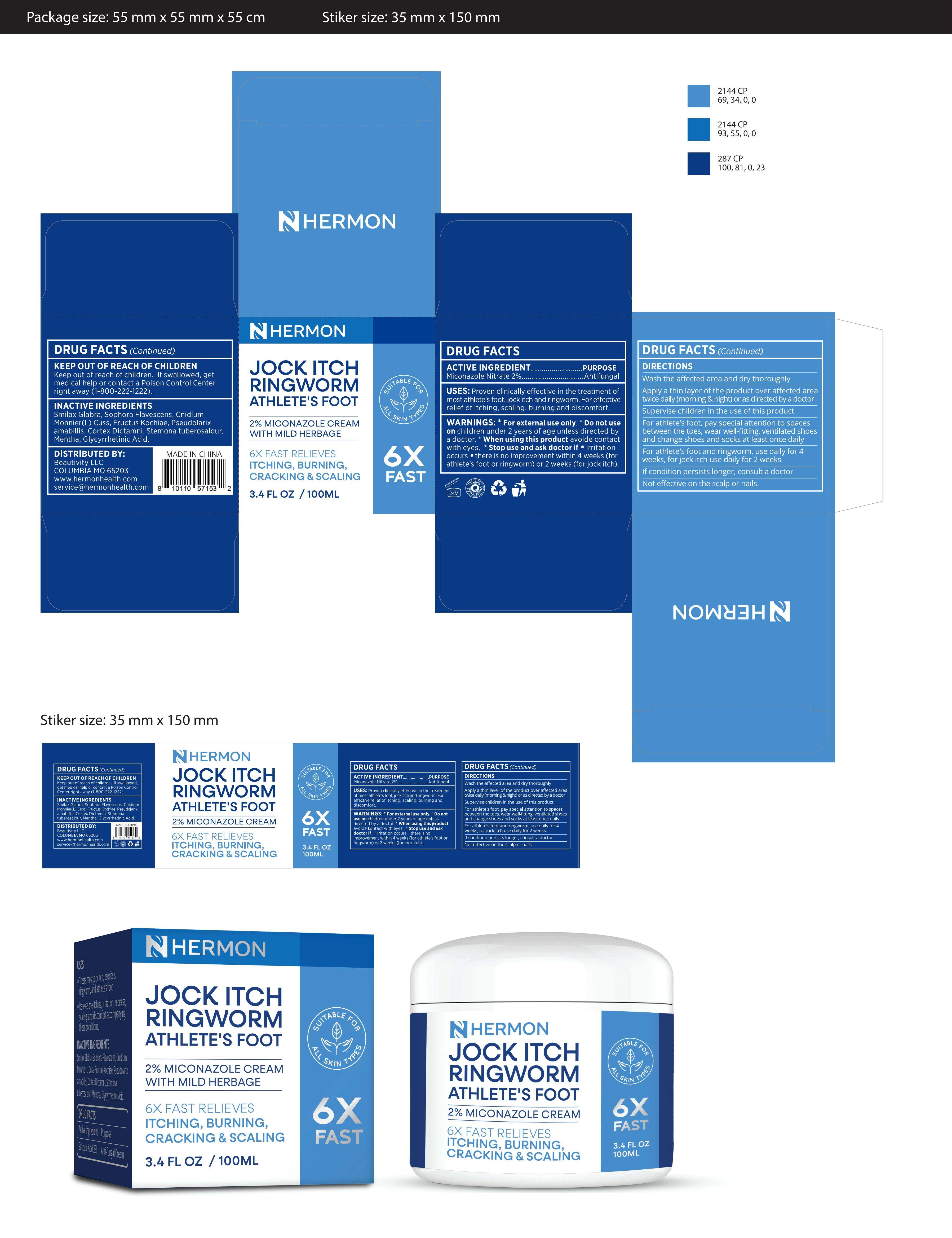 DRUG LABEL: Hermon Jock Itch Ringworm and athlete s foot cream
NDC: 84746-008 | Form: CREAM
Manufacturer: Shandong Yuyaotang Pharmaceutical Co., Ltd
Category: otc | Type: HUMAN OTC DRUG LABEL
Date: 20250402

ACTIVE INGREDIENTS: MICONAZOLE NITRATE 2 g/100 g
INACTIVE INGREDIENTS: CNIDIUM MONNIERI WHOLE; GLYCYRRHETINIC ACID; RUBUS CHINGII WHOLE; PERIPLOCA SEPIUM WHOLE; SMILAX GLABRA WHOLE; PSEUDOLARIX AMABILIS WHOLE; STEMONA TUBEROSA WHOLE; MENTHA ARVENSIS LEAF; SOPHORA FLAVESCENS WHOLE

84746-008

Active Ingredient

Miconazole Nitrate 2%

Purpose

Antifungal

Use

Proven clinically effective in the treatment of most athlete's foot, jock itch and ringworm. For effective relief of itching, scaling, burning and discomfort

Warnings

For external use only.

Do not use on children under 2 years of age unless directed by a doctor.

When Using

When using this product avoide contact with eyes

Stop Use

Stop use if irritation occurs there is no improvement within 4 weeks (for athlete's foot or ringworm) or 2 weeks (for jock itch)

Ask Doctor

If condition persists longer, consult a doctor

Keep Oot Of Reach Of Children

Keep out of reach of children. If swallowed, get medical help or contact a Poison Control Center right away (1-800-222-1222).

Directions

-wash the affected area and dry thoroughly
-apply a thin layer of the product over affected area twice daily (morning and night) or as directed by a doctor
-supervise children in the use of this product
-for athlete's foot, pay special attention to spaces between the toes, wear well-fitting, ventilated shoes and change shoes and socks at least once daily
-for athlete's foot and ringworm, use daily for 4 weeks, for jock itch use daily for 2 weeks
-if condition persists longer, consult a doctor
not effective on the scalp or nails

Other information

Store at 59-86℉ （15-30℃）
Close the cap tightly after use.

Inactive ingredients

Smilax Glabra, Sophora Flavescens, Cnidium Monnier(L)Cuss, Fructus Kochiae, Pseudolarixamabillis,Cortex Dictamni,Stemona tuberosalour，Mentha, Glycyrrhetinic Acid.

Questions

service@hermonhealth.com